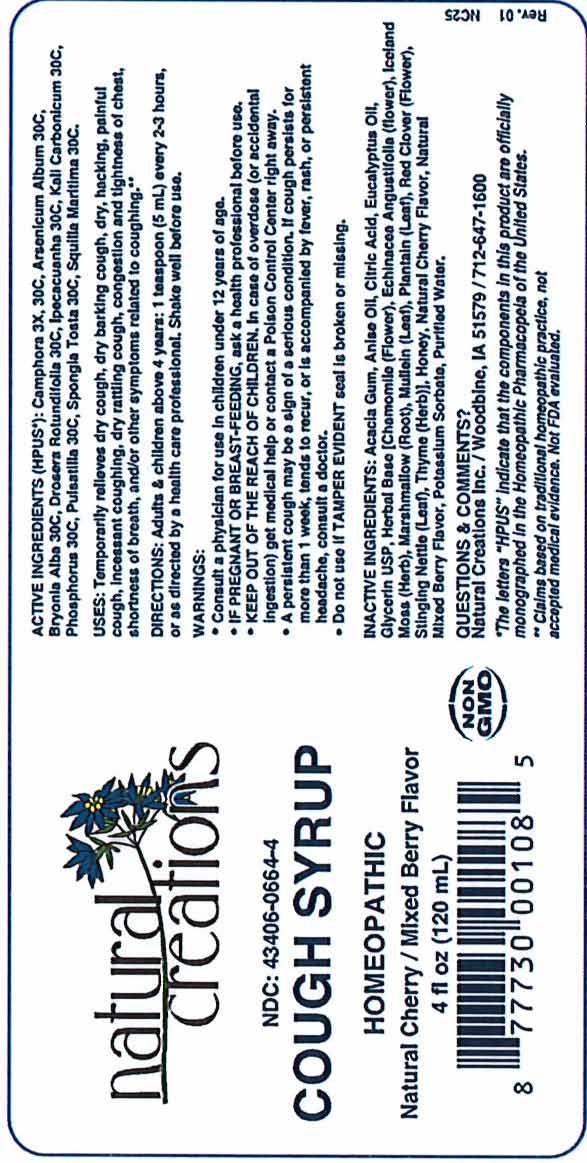 DRUG LABEL: Cough Syrup
NDC: 43406-0664 | Form: SYRUP
Manufacturer: Natural Creations, Inc.
Category: homeopathic | Type: HUMAN OTC DRUG LABEL
Date: 20221219

ACTIVE INGREDIENTS: CAMPHOR (NATURAL) 30 [hp_C]/1 mL; ARSENIC TRIOXIDE 30 [hp_C]/1 mL; BRYONIA ALBA ROOT 30 [hp_C]/1 mL; DROSERA ROTUNDIFOLIA 30 [hp_C]/1 mL; IPECAC 30 [hp_C]/1 mL; POTASSIUM CARBONATE 30 [hp_C]/1 mL; PHOSPHORUS 30 [hp_C]/1 mL; ANEMONE PULSATILLA 30 [hp_C]/1 mL; SPONGIA OFFICINALIS SKELETON, ROASTED 30 [hp_C]/1 mL; DRIMIA MARITIMA WHOLE 30 [hp_C]/1 mL
INACTIVE INGREDIENTS: ACACIA; ANISE OIL; CITRIC ACID MONOHYDRATE; EUCALYPTUS OIL; GLYCERIN; CHAMOMILE; ECHINACEA ANGUSTIFOLIA; CETRARIA ISLANDICA SUBSP. ISLANDICA; ALTHAEA OFFICINALIS ROOT; MULLEIN LEAF; MUSA X PARADISIACA LEAF; RED CLOVER; URTICA DIOICA LEAF; THYME; HONEY; POTASSIUM SORBATE; WATER

COUGH SYRUP

ACTIVE INGREDIENT

ACTIVE INGREDIENTS (HPUS*): Camphora 3X, 30C, Arsenicum Album 30C, Bryonia Alba 30C, Drosera Rotundifolia 30C, Ipecacuanha 30C, Kali Carbonicum 30C, Phosphorus 30C, Pulsatilla 30C, Spongia Tosta 30C, Squilla Maritima 30C.

INDICATIONS AND USAGE

USES: Temporarily relieves dry cough, dry barking cough, dry, hacking, painful cough, incessant coughing, dry rattling cough, congestion and tightness of chest, shortness of breath, and/or other symptoms related to coughing.**

PURPOSE

USES: Temporarily relieves dry cough, dry barking cough, dry, hacking, painful cough, incessant coughing, dry rattling cough, congestion and tightness of chest, shortness of breath, and/or other symptoms related to coughing.**

DOSAGE AND ADMINISTRATION

DIRECTIONS: Adults & children above 4 years: 1 teaspoon (5mL) every 2-3 hours, or as directed by a health care professional. Shake well before use.

KEEP OUT OF REACH OF CHILDREN

KEEP OUT OF THE REACH OF CHILDREN. In case ov overdose (or accidental ingestion) get medical help or contact a Poison Control Center right away.

WARNINGS:

- Consult a physician for use in children under 12 years of age.
- IF PREGNANT OR BREAST-FEEDING, ask a health professional before use.
- KEEP OUT OF THE REACH OF CHILDREN. In case of overdose (or accidental ingestion) get medical help or contact a Poison Control Center right away.
- Do not use if TAMPER EVIDENT seal is broken or missing.

INACTIVE INGREDIENT

INACTIVE INGREDIENTS: Acacia Gum, Anise Oil, Citric Acid, Eucalyptus Oil, Glycerin, Herbal Base [Chamomile (flower), Echinacea Angustifolia (Flower), Iceland Moss (Herb), Marshmallow (Root), Mullein (Leaf), Plantain (Leaf), Red Clover (Flower), Stinging Nettle (Leaf), Thyme (Herb)], Honey, Natural Cherry Flavor, Natural Mixed Berry Flavor, Potassium Sorbate, Purified Water.

QUESTIONS & COMMENTS?

Natural Creations, Inc. / Woodbine, IA 51579 / 712-647-1600

REFERENCES

*The letters "HPUS" indicate the components in this product are officially monographed in the Homeopathic Pharmacopeia of the United States.

**These statements have not been reviewed by the FDA. They are based on traditional homeopathic practice.

PACKAGE LABEL

NDC: 43406-0664-4

COUGH SYRUP

HOMEOPATHIC

Natural Cherry / Mixed Berry Flavor

4 fl oz (120 mL)